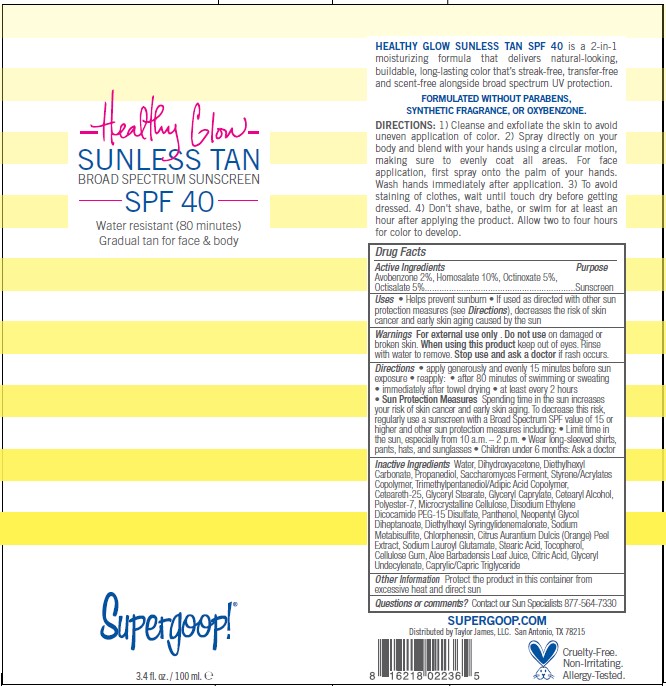 DRUG LABEL: HEALTHY GLOW SUNLESS TAN BROAD SPECTRUM SUNSCREEN
NDC: 75936-514 | Form: SPRAY
Manufacturer: Supergoop, LLC
Category: otc | Type: HUMAN OTC DRUG LABEL
Date: 20230126

ACTIVE INGREDIENTS: AVOBENZONE 2 g/100 mL; HOMOSALATE 10 g/100 mL; OCTINOXATE 5 g/100 mL; OCTISALATE 5 g/100 mL
INACTIVE INGREDIENTS: STEARIC ACID; GLYCERYL 1-UNDECYLENATE; ORANGE PEEL; TOCOPHEROL; ALOE VERA LEAF; ANHYDROUS CITRIC ACID; CHLORPHENESIN; DIETHYLHEXYL SYRINGYLIDENEMALONATE; SODIUM METABISULFITE; MEDIUM-CHAIN TRIGLYCERIDES; NEOPENTYL GLYCOL DIHEPTANOATE; PANTHENOL; WATER; DIHYDROXYACETONE; DIETHYLHEXYL CARBONATE; PROPANEDIOL; SACCHAROMYCES LYSATE; STYRENE/ACRYLAMIDE COPOLYMER (MW 500000); TRIMETHYLPENTANEDIOL/ADIPIC ACID/GLYCERIN CROSSPOLYMER (25000 MPA.S); CETEARETH-25; GLYCERYL MONOSTEARATE; GLYCERYL CAPRYLATE; CETOSTEARYL ALCOHOL; POLYESTER-7; MICROCRYSTALLINE CELLULOSE; DISODIUM ETHYLENE DICOCAMIDE PEG-15 DISULFATE; SODIUM LAUROYL GLUTAMATE; CARBOXYMETHYLCELLULOSE SODIUM, UNSPECIFIED

Supergoop (as PLD) - Healthy Glow Sunless Tan SPF-40 (75936-5124)

ACTIVE INGREDIENTS

Avobenzone 2%

Homosalate 10%

Octinoxate 5%

Octisalate 5%

PURPOSE

SUNSCREEN

USES

- Helps prevent sunburn
- If used as directed with other sun protection measures (see Directions), decreases the risk of skin cancer and early skin aging caused by the sun

WARNINGS

For external use only . Do not use on damaged or broken skin. When using this product keep out of eyes. Rinse with water to remove. Stop use and ask a doctor if rash occurs.

KEEP OUT OF REACH OF CHILDREN.

DIRECTIONS

- apply generously and evenly 15 minutes before sun exposure
- reapply:
- after 80 minutes of swimming or sweating
- immediately after towel drying
- at least every 2 hours

- Sun Protection Measures Spending time in the sun increases your risk of skin cancer and early skin aging. To decrease this risk,

regularly use a sunscreen with a Broad Spectrum SPF value of 15 or higher and other sun protection measures including: • Limit time in the sun, especially from 10 a.m. – 2 p.m.

- Wear long-sleeved shirts, pants, hats, and sunglasses
- Children under 6 months: Ask a doctor

INACTIVE INGREDIENTS

Water, Dihydroxyacetone, Diethylhexyl Carbonate, Propanediol, Saccharomyces Ferment, Styrene/Acrylates Copolymer, Trimethylpentanediol/Adipic Acid Copolymer, Ceteareth-25, Glyceryl Stearate, Glyceryl Caprylate, Cetearyl Alcohol, Polyester-7, Microcrystalline Cellulose, Disodium Ethylene Dicocamide PEG-15 Disulfate, Panthenol, Neopentyl Glycol Diheptanoate, Diethylhexyl Syringylidenemalonate, Sodium Metabisulfite, Chlorphenesin, Citrus Aurantium Dulcis (Orange) Peel Extract, Sodium Lauroyl Glutamate, Stearic Acid, Tocopherol, Cellulose Gum, Aloe Barbadensis Leaf Juice, Citric Acid, Glyceryl Undecylenate, Caprylic/Capric Triglyceride

OTHER INFORMATION

Protect the product in this container from excessive heat and direct sun

QUESTIONS OR COMMENTS?

Contact our Sun Specialists 877-564-7330